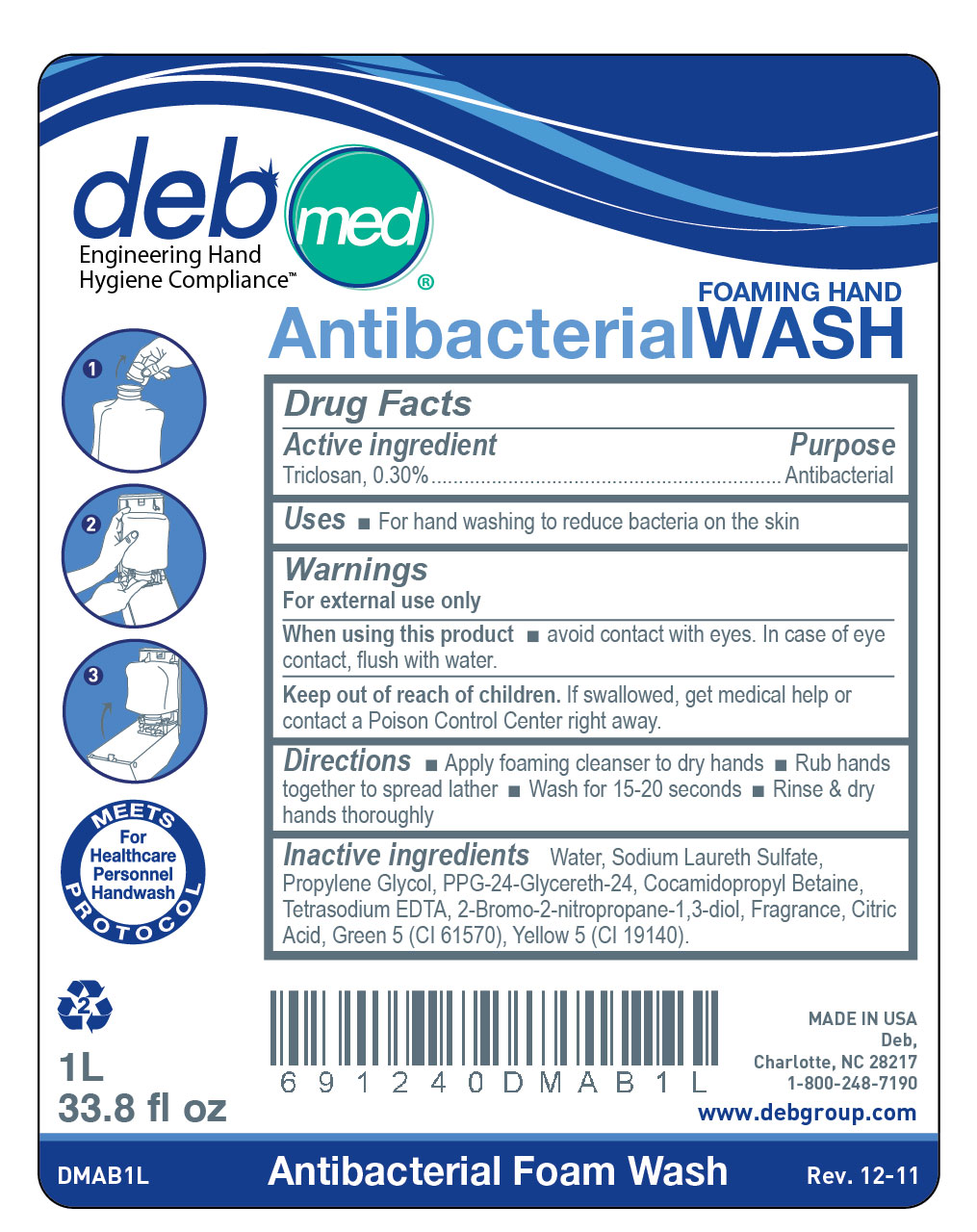 DRUG LABEL: Deb Med Antibacterial Foam Hand Wash
NDC: 11084-116 | Form: LIQUID
Manufacturer: Deb USA, Inc.
Category: otc | Type: HUMAN OTC DRUG LABEL
Date: 20120202

ACTIVE INGREDIENTS: TRICLOSAN 0.30 mL/100 mL
INACTIVE INGREDIENTS: WATER; SODIUM LAURETH SULFATE; PROPYLENE GLYCOL; COCAMIDOPROPYL BETAINE; EDETATE SODIUM; CITRIC ACID MONOHYDRATE; D&C GREEN NO. 5; FD&C YELLOW NO. 5

Drug Facts

Active ingredient

Triclosan, 0.30%

Purpose

Antibacterial

Uses

For handwashing to reduce bacteria on the skin

Warnings

For external use only

When using this product avoid contact with eyes.

In case of eye contact, flush with water.

Keep out of reach of children.

If swallowed, get medical help or contact a Poison Control right away.

Directions

Apply foam cleanser to dry hands.

Rub hands together to spread lather

Wash for 15-20 seconds

Rinse and dry hands thoroughly

Inactive ingredients

Water, Sodium Laureth Sulfate, Propylene Glycol, PPG-24-Glycereth-24, Cocamidopropyl Betaine, Tetrasodium EDTA, 2-bromo-2-nitropropane-1,3-diol, Fragrance, Citric Acid, Green 5 (CI 61570), Yellow 5 (CI 19140)

PACKAGE LABEL

deb med

Engineering Hand Hygiene Compliance

Antibacterial Foaming Hand Soap

Meets Protocol for Healthcare Personnel Handwash

1L 33.8 fl. oz.

DMAB1L

Antibacterial Foam Wash

Rev. 12-11

Made in USA

Deb, Charlotte, NC 28217

1-800-248-7190

www.debgroup.com